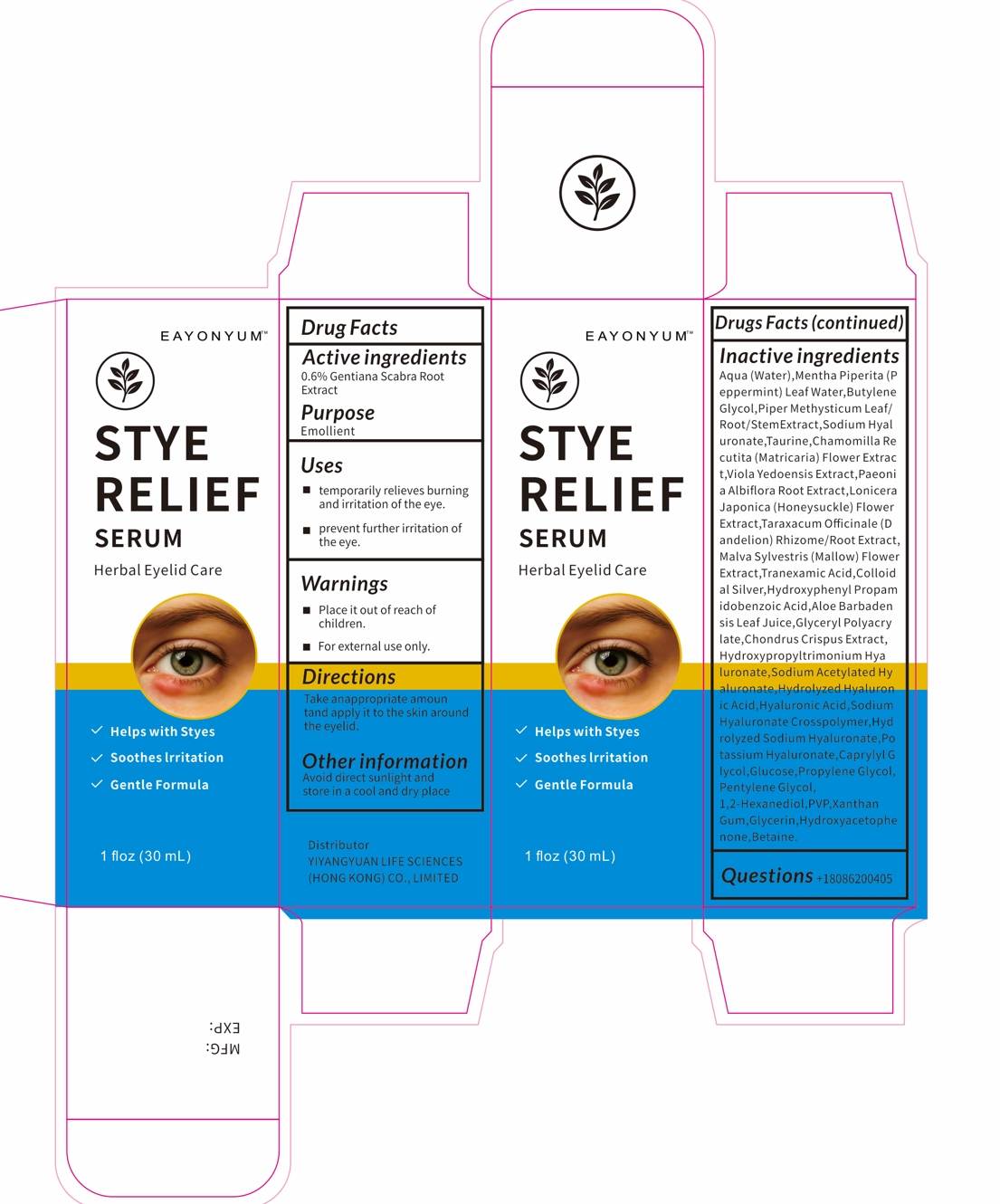 DRUG LABEL: EAYONYUM STYE RELIEF SERUM
NDC: 87267-001 | Form: LIQUID
Manufacturer: YIYANGYUAN LIFE SCIENCES (HONG KONG) CO., LIMITED
Category: otc | Type: HUMAN OTC DRUG LABEL
Date: 20251208

ACTIVE INGREDIENTS: GENTIANA SCABRA ROOT 0.6 g/100 mL
INACTIVE INGREDIENTS: LONICERA JAPONICA FLOWER; PROPYLENE GLYCOL; BETAINE; MATRICARIA CHAMOMILLA WHOLE; HYDROXYPHENYL PROPAMIDOBENZOIC ACID; TAURINE; XANTHAN GUM; CHONDRUS CRISPUS CARRAGEENAN; 1,2-HEXANEDIOL; HYDROXYACETOPHENONE; VIOLA PHILIPPICA WHOLE; TRANEXAMIC ACID; MENTHA PIPERITA (PEPPERMINT) LEAF; TARAXACUM OFFICINALE (DANDELION) ROOT; MALVA SYLVESTRIS FLOWER; WATER; DIHYDROXYPROPYLTRIMONIUM; GLUCOSE; PVP; BUTYLENE GLYCOL; ALOE BARBADENSIS LEAF JUICE; HYALURONATE SODIUM; PAEONIA LACTIFLORA ROOT; HYALURONIC ACID; CAPRYLYL GLYCOL; GLYCERIN; SODIUM ACETYLATED HYALURONATE; COLLOIDAL SILVER; PIPER METHYSTICUM ROOT

87267-001 EAYONYUM STYE RELIEF SERUM

ACTIVE INGREDIENT

Gentiana Scabra Root Extract 0.6%

PURPOSE

Emollient

INDICATIONS AND USAGE

temporarily relieves burning and irritation of the eye.
prevent further irritation of the eye.

WARNINGS

Place it out of reach of children.
For external use only.

Pregnant women and children should not use it

WHEN USING

Place it out of reach of children.

STOP USE

If you feel uncomfortable while using, please stop using.

Place it out of reach of children.

DOSAGE AND ADMINISTRATION

Take anappropriate amoun tand apply it to the skin around the eyelid.

INACTIVE INGREDIENT

Aqua (Water)
Mentha Piperita (Peppermint) Leaf Water
Butylene Glycol
Piper Methysticum Leaf/Root/Stem Extract
Sodium Hyaluronate
Taurine
Chamomilla Recutita (Matricaria) Flower Extract
Viola Yedoensis Extract
Paeonia Albiflora Root Extract
Lonicera Japonica (Honeysuckle) Flower Extract
Taraxacum Officinale (Dandelion) Rhizome/Root Extract
Malva Sylvestris (Mallow) Flower Extract
Tranexamic Acid
Colloidal Silver
Hydroxyphenyl Propamidobenzoic Acid
Aloe Barbadensis Leaf Juice
Glyceryl Polyacrylate
Chondrus Crispus Extract
Hydroxypropyltrimonium Hyaluronate
Sodium Acetylated Hyaluronate
Hydrolyzed Hyaluronic Acid
Hyaluronic Acid
Sodium Hyaluronate Crosspolymer
Hydrolyzed Sodium Hyaluronate
Potassium Hyaluronate
Caprylyl Glycol
Glucose
Propylene Glycol
Pentylene Glycol
1,2-Hexanediol
PVP
Xanthan Gum
Glycerin
Hydroxyacetophenone
Betaine